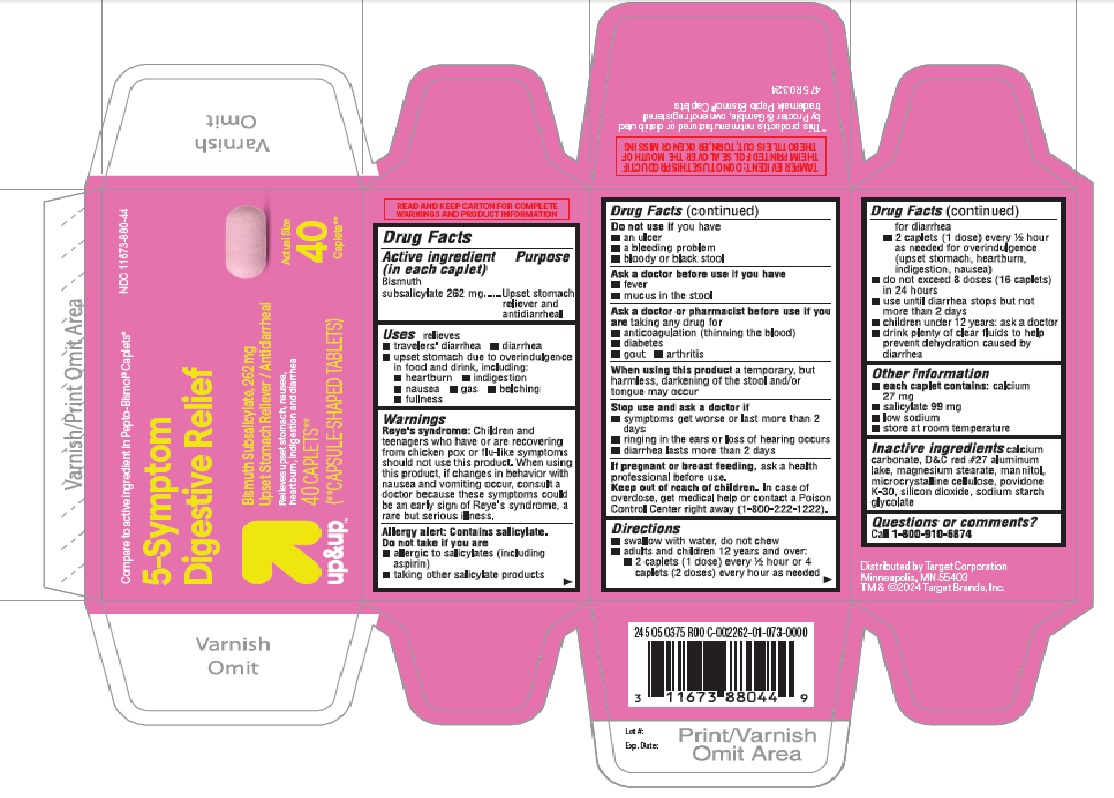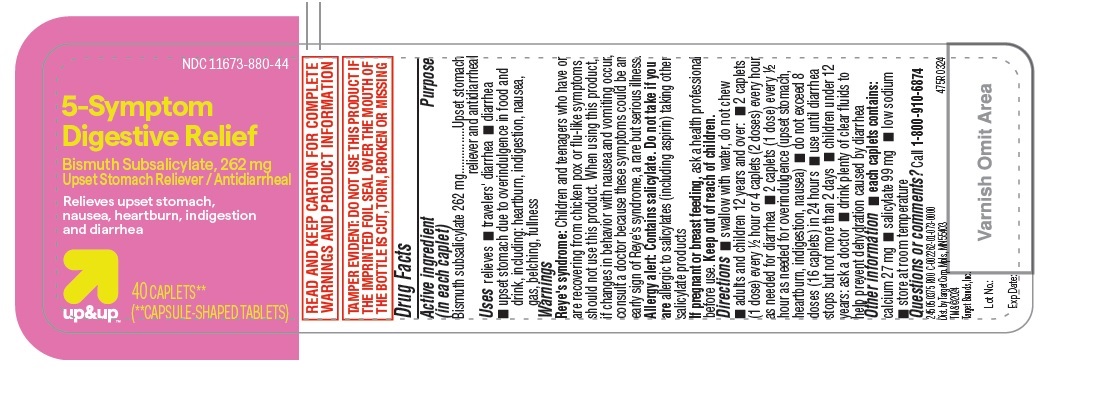 DRUG LABEL: 5-Symptom Digestive Relief
NDC: 11673-880 | Form: TABLET
Manufacturer: TARGET CORPORATION
Category: otc | Type: HUMAN OTC DRUG LABEL
Date: 20240626

ACTIVE INGREDIENTS: BISMUTH SUBSALICYLATE 262 mg/1 1
INACTIVE INGREDIENTS: POVIDONE K30; MANNITOL; SILICON DIOXIDE; D&C RED NO. 27 ALUMINUM LAKE; SODIUM STARCH GLYCOLATE TYPE A; MAGNESIUM STEARATE; CALCIUM CARBONATE; MICROCRYSTALLINE CELLULOSE

Target Bismuth subsalicylate caplets 262mg

Active ingredient (in each caplet)

Bismuth subsalicylate 262 mg

Purpose

Upset stomach reliever and antidiarrheal

Uses

relieves

- travelers' diarrhea
- diarrhea
- upset stomach due to overindulgence in food and drink, including:

-heartburn
-indigestion
-nausea
-gas
-belching
-fullness

Warnings

Reye's syndrome: Children and teenagers who have or are recovering from chicken pox or flu-like symptoms should not use this product. When using this product, if changes in behavior with nausea and vomiting occur, consult a doctor because these symptoms could be an early sign of Reye's syndrome, a rare but serious illness.

Allergy alert: Contains salicylate. Do not take if you are

- allergic to salicylates (including aspirin)
- taking other salicylate products

Do not use if you have

- an ulcer
- a bleeding problem
- bloody or black stool

Ask a doctor before use if you have

- fever
- mucus in the stool

Ask a doctor or pharmacist before use if you are taking any drug for

- anticoagulation (thinning the blood)
- diabetes
- gout
- arthritis

When using this product

a temporary, but harmless, darkening of the stool and/or tongue may occur

Stop use and ask a doctor if

- symptoms get worse or last more than 2 days
- ringing in the ears or loss of hearing occurs
- diarrhea lasts more than 2 days

If pregnant or breast feeding,

ask a health professional before use.

OVERDOSAGE

In case of overdose, get medical help or contact a Poison Control Center right away (1-800-222-1222).

Directions

- swallow with water, do not chew
- adults and children 12 years and over:

-2 caplets (1 dose) every ½ hour or 4 caplets (2 doses) every hour as needed for diarrhea
-2 caplets (1 dose) every ½ hour as needed for overindulgence (upset stomach, heartburn, indigestion, nausea)

- do not exceed 8 doses (16 caplets) in 24 hours
- use until diarrhea stops but not more than 2 days
- children under 12 years: ask a doctor
- drink plenty of clear fluids to help prevent dehydration caused by diarrhea

Other information

- each caplet contains: calcium 27 mg
- salicylate 99 mg
- low sodium
- store at room temperature

Inactive ingredients

calcium carbonate, D&C red #27 aluminum lake, magnesium stearate, mannitol, microcrystalline cellulose, povidone K-30, silicon dioxide, sodium starch glycolate

Questions or comments?

Call 1-877-290-4008